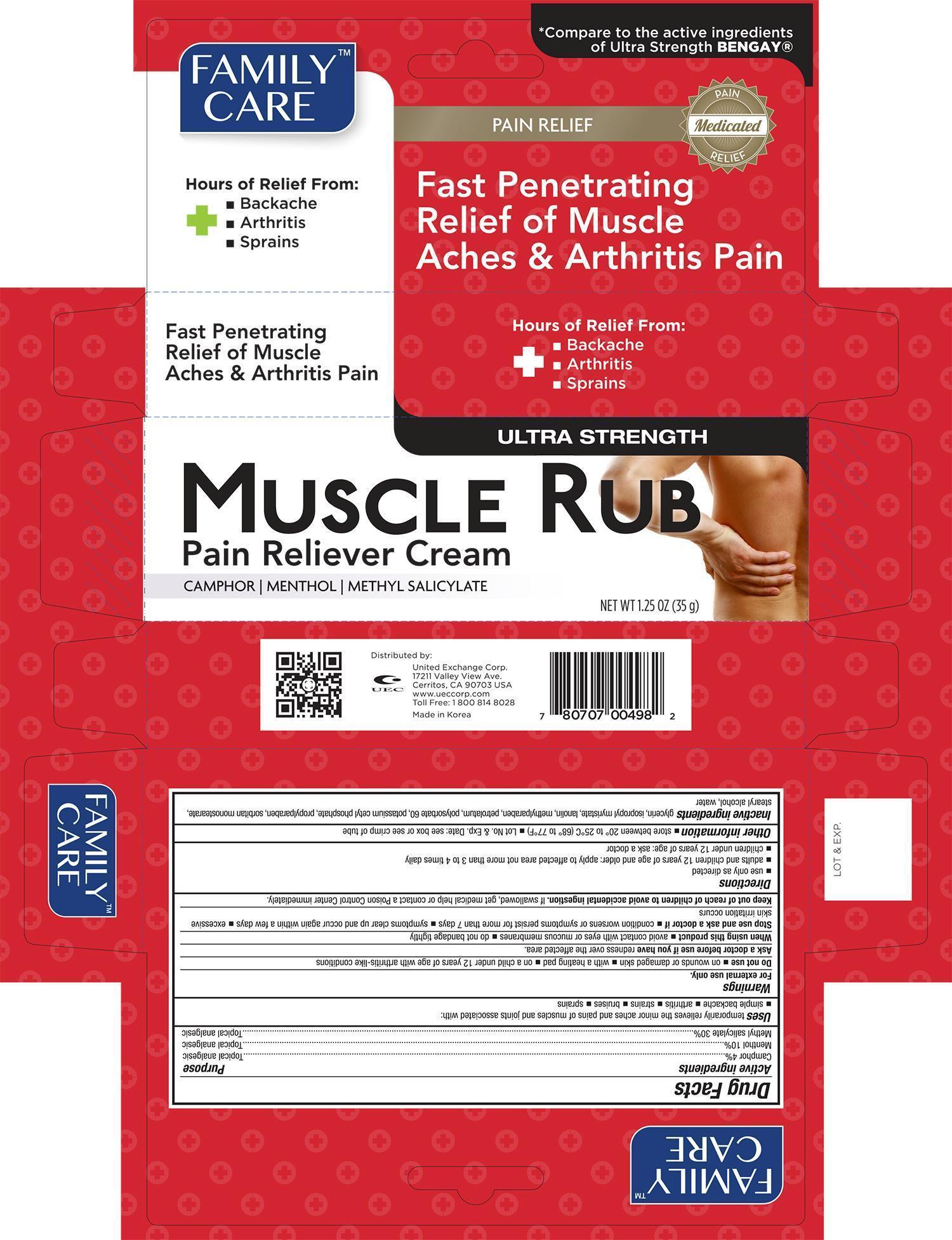 DRUG LABEL: FAMILY CARE MUSCLE RUB PAIN RELIEVER
NDC: 65923-498 | Form: CREAM
Manufacturer: UNITED EXCHANGE CORP
Category: otc | Type: HUMAN OTC DRUG LABEL
Date: 20141124

ACTIVE INGREDIENTS: MENTHOL 10 g/100 g; METHYL SALICYLATE 15 g/100 g
INACTIVE INGREDIENTS: CARBOMER HOMOPOLYMER TYPE C; CETYL ALCOHOL; OLETH-3 PHOSPHATE; STEARIC ACID; WATER

Active ingredient Purpose

Menthol- 10%, Methyl Salicylate- 15%............................................................External Analgesic

Uses

- For the temporary relief of minor aches and pains of muscles and joints

Warnings

For external use only. Use only as directed.

Keep out of reach of children to avoid accidental poisoning.

DO NOT USE

Discontinue use if excessive irritation of the skin develops.

Do not bandage tightly, apply to wounds or damaged skin or use with a heating pad.

ASK DOCTOR

If condition worsens, or if symptoms persist for more than 7 days or clear-up and occur again within a few days, discontinue use of this product and consult a doctor.

WHEN USING

Avoid contact with eyes or mucous membranes.

Directions

- Adults and children 2 years of age and older: Apply to affected area not more than 3 to 4 times daily.
- Children under 2 years of age: Consult a doctor.

Other information

- Store at controlled room temperature 15-30 C (59-86 F)

Inactive ingredients

Carbopol 940, Cetyl Alcohol, Oleth-3 Phosphate, Stearic Acid, Triethanolmine, Water

DOSAGE AND ADMINISTRATION

Distributed by: UNITED EXCHANGE CORP. 17211 Valley View Ave, Cerritos, CA 90703 USA

Made in Korea